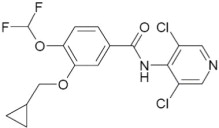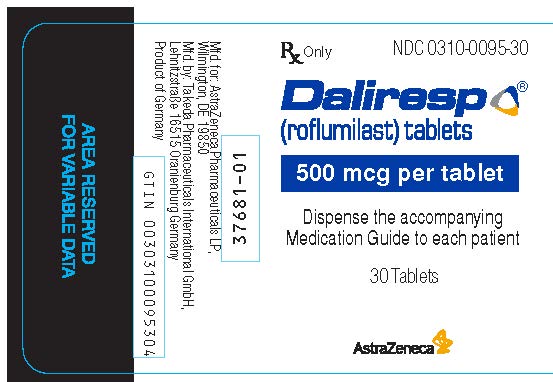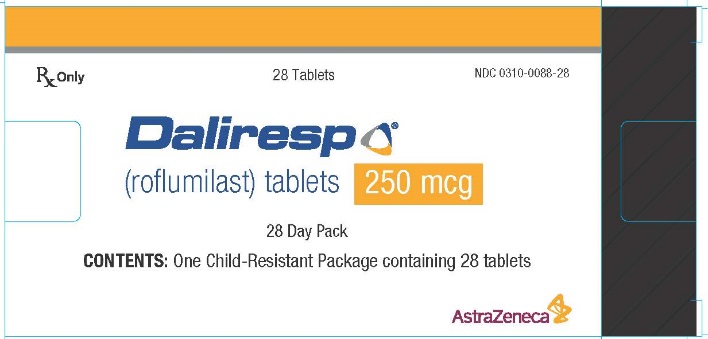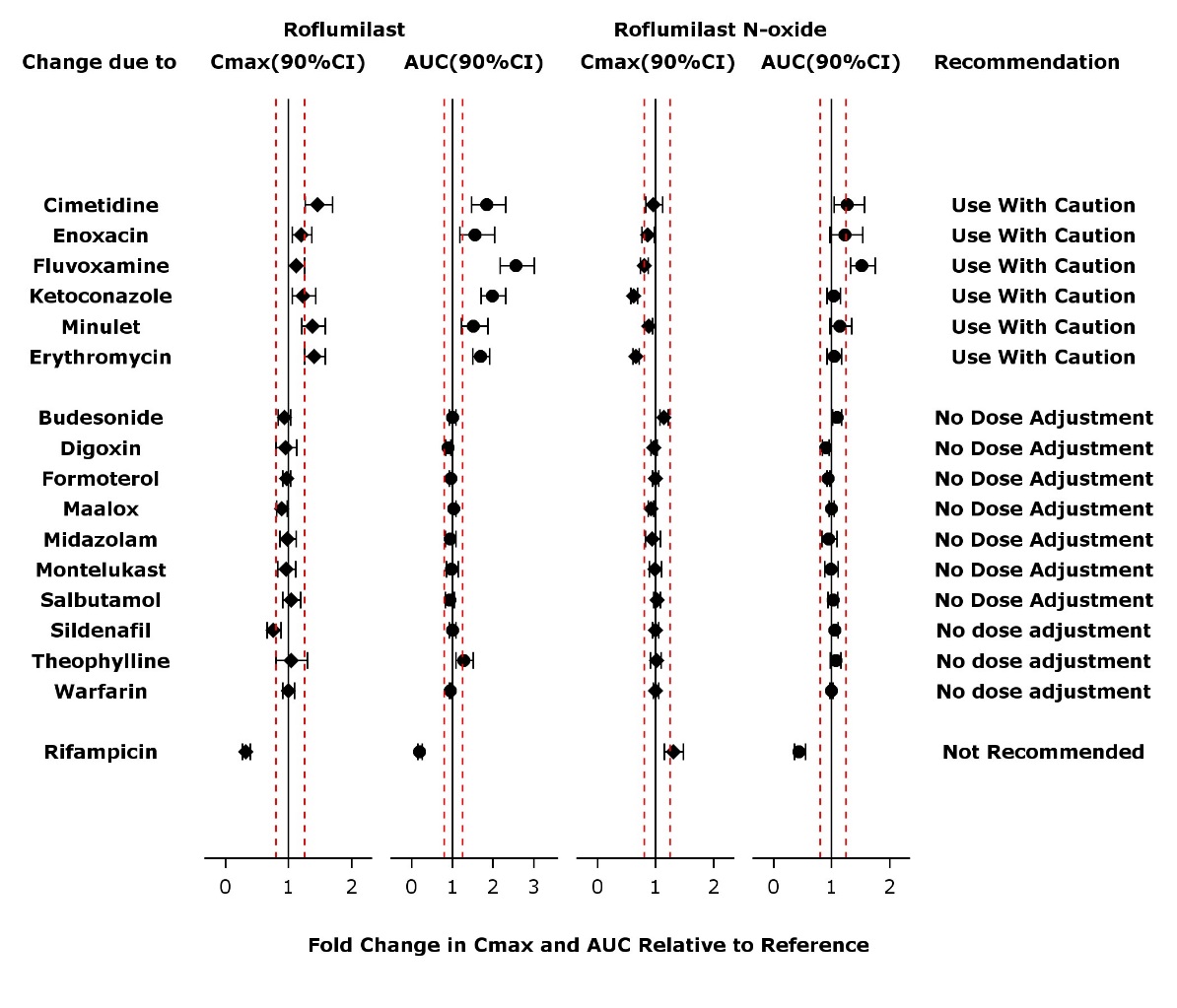 DRUG LABEL: Daliresp
NDC: 0310-0095 | Form: TABLET
Manufacturer: AstraZeneca Pharmaceuticals LP
Category: prescription | Type: HUMAN PRESCRIPTION DRUG LABEL
Date: 20200312

ACTIVE INGREDIENTS: roflumilast 500 ug/1 1
INACTIVE INGREDIENTS: lactose monohydrate; starch, corn; POVIDONE, UNSPECIFIED; magnesium stearate

HIGHLIGHTS OF PRESCRIBING INFORMATION

These highlights do not include all the information needed to use DALIRESP safely and effectively. See full prescribing information for DALIRESP.
DALIRESP® (roflumilast) tablets
Initial U.S. Approval: 2011

1 INDICATIONS AND USAGE

DALIRESP is a selective phosphodiesterase 4 inhibitor indicated as a treatment to reduce the risk of COPD exacerbations in patients with severe COPD associated with chronic bronchitis and a history of exacerbations. (1, 14)

Limitations of Use:

- DALIRESP is not a bronchodilator and is not indicated for the relief of acute bronchospasm. (1,14)
- DALIRESP 250 mcg is a starting dose, for the first 4 weeks of treatment only and is not the effective (therapeutic) dose. (2,14)

2 DOSAGE AND ADMINISTRATION

The maintenance dose for patients with COPD is one 500 mcg tablet per day, with or without food. Starting treatment with a dose of DALIRESP 250 mcg once daily for 4 weeks and increasing to DALIRESP 500 mcg once daily thereafter may reduce the rate of treatment discontinuation in some patients. (2)

3 DOSAGE FORMS AND STRENGTHS

Tablets: 250 mcg, 500 mcg (3)

4 CONTRAINDICATIONS

Moderate to severe liver impairment (Child-Pugh B or C) (4)

5 WARNINGS AND PRECAUTIONS

- Acute Bronchospasm: Do not use for the relief of acute bronchospasm. (5.1)
- Psychiatric Events including Suicidality: Advise patients, their caregivers, and families to be alert for the emergence or worsening of insomnia, anxiety, depression, suicidal thoughts or other mood changes, and if such changes occur to contact their healthcare provider. Carefully weigh the risks and benefits of treatment with DALIRESP in patients with a history of depression and/or suicidal thoughts or behavior. (5.2)
- Weight Decrease: Monitor weight regularly. If unexplained or clinically significant weight loss occurs, evaluate weight loss and consider discontinuation of DALIRESP. (5.3)
- Drug Interactions: Use with strong cytochrome P450 enzyme inducers (e.g., rifampicin, phenobarbital, carbamazepine, phenytoin) is not recommended. (5.4)

6 ADVERSE REACTIONS

Most common adverse reactions (≥2%) are diarrhea, weight decrease, nausea, headache, back pain, influenza, insomnia, dizziness and decreased appetite. (6.1)

To report SUSPECTED ADVERSE REACTIONS, contact AstraZeneca at 1-800-236-9933 or FDA at 1-800-FDA-1088 or www.fda.gov/medwatch.

7 DRUG INTERACTIONS

Use with inhibitors of CYP3A4 or dual inhibitors of CYP3A4 and CYP1A2 (e.g., erythromycin, ketoconazole, fluvoxamine, enoxacin, cimetidine) will increase roflumilast systemic exposure and may result in increased adverse reactions. The risk of such concurrent use should be weighed carefully against benefit. (7.2)

8 USE IN SPECIFIC POPULATIONS

Nursing Mothers: DALIRESP should not be used by women who are nursing as excretion of roflumilast and/or its metabolites into human milk is probable and there are no human studies that have investigated effects of DALIRESP on breast-fed infants. (8.2)

FULL PRESCRIBING INFORMATION

1 INDICATIONS AND USAGE

DALIRESP® is indicated as a treatment to reduce the risk of COPD exacerbations in patients with severe COPD associated with chronic bronchitis and a history of exacerbations.

Limitations of Use

DALIRESP is not a bronchodilator and is not indicated for the relief of acute bronchospasm.

DALIRESP 250 mcg is a starting dose, for the first 4 weeks of treatment only and is not the effective (therapeutic) dose.

2 DOSAGE AND ADMINISTRATION

The maintenance dose of DALIRESP is one 500 micrograms (mcg) tablet per day, with or without food.

Starting treatment with a dose of DALIRESP 250 mcg once daily for 4 weeks and increasing to DALIRESP 500 mcg once daily thereafter may reduce the rate of treatment discontinuation in some patients [see Clinical Studies (14.1)]. However, 250 mcg per day is not the effective (therapeutic) dose.

3 DOSAGE FORMS AND STRENGTHS

- DALIRESP 250 mcg tablets are white to off-white, round, embossed with “D” on one side and “250” on the other side
- DALIRESP 500 mcg tablets are white to off-white, round, embossed with “D” on one side and “500” on the other side

4 CONTRAINDICATIONS

The use of DALIRESP is contraindicated in the following condition:

Moderate to severe liver impairment (Child-Pugh B or C) [see Clinical Pharmacology (12.3) and Use in Specific Populations (8.6)].

5 WARNINGS AND PRECAUTIONS

5.1 Treatment of Acute Bronchospasm

DALIRESP is not a bronchodilator and should not be used for the relief of acute bronchospasm.

5.2 Psychiatric Events including Suicidality

Treatment with DALIRESP is associated with an increase in psychiatric adverse reactions. In 8 controlled clinical trials 5.9% (263) of patients treated with DALIRESP 500 mcg daily reported psychiatric adverse reactions compared to 3.3% (137) treated with placebo. The most commonly reported psychiatric adverse reactions were insomnia, anxiety, and depression which were reported at higher rates in those treated with DALIRESP 500 mcg daily (2.4%, 1.4%, and 1.2% for DALIRESP versus 1.0%, 0.9%, and 0.9% for placebo, respectively) [see Adverse Reactions (6.1)]. Instances of suicidal ideation and behavior, including completed suicide, have been observed in clinical trials. Three patients experienced suicide-related adverse reactions (one completed suicide and two suicide attempts) while receiving DALIRESP compared to one patient (suicidal ideation) who received placebo. One patient completed suicide while receiving DALIRESP in Trial 9 [see Clinical Studies (14.1)], which assessed the effect of adding roflumilast to a fixed-dose combination (FDC) of ICS/LABA on rates of exacerbations in COPD patients over 1 year of treatment. Cases of suicidal ideation and behavior, including completed suicide, have been observed in the post-marketing setting in patients with or without a history of depression.

Before using DALIRESP in patients with a history of depression and/or suicidal thoughts or behavior, prescribers should carefully weigh the risks and benefits of treatment with DALIRESP in such patients. Patients, their caregivers, and families should be advised of the need to be alert for the emergence or worsening of insomnia, anxiety, depression, suicidal thoughts or other mood changes, and if such changes occur to contact their healthcare provider. Prescribers should carefully evaluate the risks and benefits of continuing treatment with DALIRESP if such events occur.

5.3 Weight Decrease

Weight loss was a common adverse reaction in DALIRESP clinical trials and was reported in 7.5% (331) of patients treated with DALIRESP 500 mcg once daily compared to 2.1% (89) treated with placebo [see Adverse Reactions (6.1)]. In addition to being reported as adverse reactions, weight was prospectively assessed in two placebo-controlled clinical trials of one year duration. In these studies, 20% of patients receiving roflumilast experienced moderate weight loss (defined as between 5-10% of body weight) compared to 7% of patients who received placebo. In addition, 7% of patients who received roflumilast compared to 2% of patients receiving placebo experienced severe (>10% body weight) weight loss. During follow-up after treatment discontinuation, the majority of patients with weight loss regained some of the weight they had lost while receiving DALIRESP. Patients treated with DALIRESP should have their weight monitored regularly. If unexplained or clinically significant weight loss occurs, weight loss should be evaluated, and discontinuation of DALIRESP should be considered.

5.4 Drug Interactions

A major step in roflumilast metabolism is the N-oxidation of roflumilast to roflumilast N-oxide by CYP3A4 and CYP1A2. The administration of the cytochrome P450 enzyme inducer rifampicin resulted in a reduction in exposure, which may result in a decrease in the therapeutic effectiveness of DALIRESP. Therefore, the use of strong cytochrome P450 enzyme inducers (e.g., rifampicin, phenobarbital, carbamazepine, phenytoin) with DALIRESP is not recommended [see Drug Interactions (7.1) and Clinical Pharmacology (12.3)].

6 ADVERSE REACTIONS

The following adverse reactions are described in greater detail in other sections:

- Psychiatric Events Including Suicidality [see Warnings and Precautions (5.2)]
- Weight Decrease [see Warnings and Precautions (5.3)]

6.1 Adverse Reactions in Clinical Studies

Because clinical trials are conducted under widely varying conditions, adverse reaction rates observed in the clinical trials of a drug cannot be directly compared to rates in the clinical trials of another drug and may not reflect the rates observed in practice.

The safety data described below reflect exposure of 4438 patients to DALIRESP 500 mcg once daily in four 1-year placebo-controlled trials, two 6-month placebo-controlled trials, and two 6-month drug add-on trials [see Clinical Studies (14.1)]. In these trials, 3136 and 1232 COPD patients were exposed to DALIRESP 500 mcg once daily for 6 months and 1 year, respectively.

The population had a median age of 64 years (range 40-91), 73% were male, 92.9% were Caucasian, and had COPD with a mean pre-bronchodilator forced expiratory volume in one second (FEV1) of 8.9 to 89.1% predicted. In these trials, 68.5% of the patients treated with DALIRESP reported an adverse reaction compared with 65.3% treated with placebo.

The proportion of patients who discontinued treatment due to adverse reaction was 14.8% for DALIRESP-treated patients and 9.9% for placebo-treated patients. The most common adverse reactions that led to discontinuation of DALIRESP were diarrhea (2.4%) and nausea (1.6%).

Serious adverse reactions, whether considered drug-related or not by the investigators, which occurred more frequently in DALIRESP-treated patients include diarrhea, atrial fibrillation, lung cancer, prostate cancer, acute pancreatitis, and acute renal failure.

Table 1 summarizes the adverse reactions reported by ≥2% of patients in the DALIRESP group in 8 controlled COPD clinical trials.

Table 1: Adverse Reactions Reported by ≥2% of Patients Treated with DALIRESP 500 mcg daily and Greater Than Placebo
 | Treatment
Adverse Reactions | DALIRESP | Placebo
(Preferred Term) | (N=4438) | (N=4192)
 | n (%) | n (%)
Diarrhea | 420 (9.5) | 113 (2.7)
Weight decreased | 331 (7.5) | 89 (2.1)
Nausea | 209 (4.7) | 60 (1.4)
Headache | 195 (4.4) | 87 (2.1)
Back pain | 142 (3.2) | 92 (2.2)
Influenza | 124 (2.8) | 112 (2.7)
Insomnia | 105 (2.4) | 41 (1.0)
Dizziness | 92 (2.1) | 45 (1.1)
Decreased appetite | 91 (2.1) | 15 (0.4)

Adverse reactions that occurred in the DALIRESP group at a frequency of 1 to 2% where rates exceeded that in the placebo group include:

Gastrointestinal disorders - abdominal pain, dyspepsia, gastritis, vomiting

Infections and infestations - rhinitis, sinusitis, urinary tract infection

Musculoskeletal and connective tissue disorders - muscle spasms

Nervous system disorders - tremor

Psychiatric disorders - anxiety, depression

The safety profile of roflumilast reported during Trial 9 was consistent with the key pivotal studies.

6.2 Postmarketing Experience

The following adverse reactions have been identified from spontaneous reports of DALIRESP received worldwide and have not been listed elsewhere. These adverse reactions have been chosen for inclusion due to a combination of seriousness, frequency of reporting or potential causal connection to DALIRESP. Because these adverse reactions were reported voluntarily from a population of uncertain size, it is not possible to estimate their frequency or establish a causal relationship to DALIRESP exposure: hypersensitivity reactions (including angioedema, urticaria, and rash), gynecomastia.

7 DRUG INTERACTIONS

A major step in roflumilast metabolism is the N-oxidation of roflumilast to roflumilast N-oxide by CYP3A4 and CYP1A2 [see Clinical Pharmacology (12.3)].

7.1 Drugs that Induce Cytochrome P450 (CYP) Enzymes

Strong cytochrome P450 enzyme inducers decrease systemic exposure to roflumilast and may reduce the therapeutic effectiveness of DALIRESP. Therefore the use of strong cytochrome P450 inducers (e.g., rifampicin, phenobarbital, carbamazepine, and phenytoin) with DALIRESP is not recommended [see Warnings and Precautions (5.4) and Clinical Pharmacology (12.3)].

7.2 Drugs that Inhibit Cytochrome P450 (CYP) Enzymes

The co-administration of DALIRESP (500 mcg) with CYP3A4 inhibitors or dual inhibitors that inhibit both CYP3A4 and CYP1A2 simultaneously (e.g., erythromycin, ketoconazole, fluvoxamine, enoxacin, cimetidine) may increase roflumilast systemic exposure and may result in increased adverse reactions. The risk of such concurrent use should be weighed carefully against benefit [see Clinical Pharmacology (12.3)].

7.3 Oral Contraceptives Containing Gestodene and Ethinyl Estradiol

The co-administration of DALIRESP (500 mcg) with oral contraceptives containing gestodene and ethinyl estradiol may increase roflumilast systemic exposure and may result in increased side effects. The risk of such concurrent use should be weighed carefully against benefit [see Clinical Pharmacology (12.3)].

8 USE IN SPECIFIC POPULATIONS

8.1 Pregnancy

TERATOGENIC EFFECTS

Risk Summary

There are no randomized clinical studies of DALIRESP in pregnant women. In animal reproductive toxicity studies, DALIRESP administered to pregnant rats and rabbits during the period of organogenesis produced no fetal structural abnormalities. The highest DALIRESP dose in these studies was approximately 30 and 26 times, respectively, the maximum recommended human dose (MRHD). DALIRESP induced post-implantation loss in rats at doses greater than or equal to approximately 10 times the MRHD. DALIRESP induced stillbirth and decreased pup viability in mice at doses corresponding to approximately 16 and 49 times, respectively, the MRHD. DALIRESP has been shown to adversely affect pup post-natal development when dams were treated with the drug during pregnancy and lactation periods in mice at doses corresponding to 49 times the MRHD (see Data).

The background risk of major birth defects and miscarriage for the indicated population is unknown. In the U.S. general population, the estimated background risk of major birth defects and miscarriage in clinically recognized pregnancies is 2 to 4% and 15 to 20%, respectively.

Clinical Considerations

Labor and delivery

DALIRESP should not be used during labor and delivery. There are no human studies that have investigated effects of DALIRESP on preterm labor or labor at term; however, animal studies showed that DALIRESP disrupted the labor and delivery process in mice.

Data

Animal data

In an embryo-fetal development study, pregnant rats were dosed orally during the period of organogenesis with up to 1.8 mg/kg/day DALIRESP (approximately 30 times the MRHD on an AUC basis). No evidence of structural abnormalities or effects on survival rates were observed. DALIRESP did not affect embryo-fetal development at approximately 3 times the MRHD (on a mg/m^2 basis at a maternal oral dose of 0.2 mg/kg/day).

In a fertility and embryo-fetal development study, male rats were dosed orally with up to 1.8 mg/kg/day DALIRESP for 10 weeks and females for two weeks prior to pairing and throughout the organogenesis period. DALIRESP induced pre- and post-implantation loss at doses greater than or equal to approximately 10 times the MRHD (on a mg/m2 basis at maternal oral doses greater than or equal to 0.6 mg/kg/day). DALIRESP did not cause fetal structural abnormalities at exposures up to approximately 29 times the MRHD (on an AUC basis at maternal oral doses up to 1.8 mg/kg/day).

In an embryo-fetal development study in rabbits, pregnant does were dosed orally with 0.8 mg/kg/day DALIRESP during the period of organogenesis. DALIRESP did not cause fetal structural abnormalities at exposures approximately 26 times the MRHD (on a mg/m^2 basis at maternal oral doses of 0.8 mg/kg/day).

In pre- and post-natal developmental studies in mice, dams were dosed orally with up to 12 mg/kg/day

DALIRESP during the period of organogenesis and lactation. DALIRESP induced stillbirth and decreased pup

viability at doses corresponding to approximately 16 and 49 times, respectively, the MRHD (on a mg/m^2

basis at maternal doses >2 mg/kg/day and 6 mg/kg/day, respectively). DALIRESP induced delivery retardation in pregnant mice at doses greater or equal to approximately 16 times the MRHD (on a mg/m^2 basis at maternal doses >2 mg/kg/day). DALIRESP decreased pup rearing frequencies at approximately 49 times the MRHD (on a mg/m^2 basis at a maternal dose of 6 mg/kg/day) during pregnancy and lactation. DALIRESP also decreased survival and forelimb grip reflex and delayed pinna detachment in mouse pups at approximately 97 times the MRHD (on a mg/m^2 basis at a maternal dose of 12 mg/kg/day).

8.2 Lactation

Risk Summary

There is no information regarding the presence of DALIRESP in human milk, the effects on the breastfed infant, or the effects on milk production.

Roflumilast and/or its metabolites are excreted into the milk of lactating rats. Excretion of roflumilast and/or its metabolites into human milk is probable. DALIRESP should not be used by women who are nursing.

Data

Animal data

Roflumilast and/or its metabolite concentrations measured 8 hours after an oral dose of 1 mg/kg given to lactating rats were 0.32 and 0.02 mcg/g in the milk and pup liver, respectively.

8.4 Pediatric Use

COPD does not normally occur in children. The safety and effectiveness of DALIRESP in pediatric patients have not been established.

8.5 Geriatric Use

Of the 4438 COPD subjects exposed to DALIRESP for up to 12 months in 8 controlled clinical trials, 2022 were >65 years of age and 471 were >75 years of age. No overall differences in safety or effectiveness were observed between these subjects and younger subjects and other reported clinical experience has not identified differences in responses between the elderly and younger patients, but greater sensitivity of some older individuals cannot be ruled out. Based on available data for roflumilast, no adjustment of dosage in geriatric patients is warranted [see Clinical Pharmacology (12.3)].

8.6 Hepatic Impairment

Roflumilast 250 mcg once daily for 14 days was studied in subjects with mild-to-moderate hepatic impairment classified as Child-Pugh A and B (8 subjects in each group). The AUCs of roflumilast and roflumilast N-oxide were increased by 51% and 24%, respectively, in Child-Pugh A subjects and by 92% and 41%, respectively, in Child-Pugh B subjects, as compared to age-, weight-, and gender-matched healthy subjects. The Cmax of roflumilast and roflumilast N-oxide were increased by 3% and 26%, respectively in Child-Pugh A subjects and by 26% and 40%, respectively in Child-Pugh B subjects, as compared to healthy subjects. DALIRESP 500 mcg has not been studied in hepatically impaired patients. Clinicians should consider the risk-benefit of administering DALIRESP to patients who have mild liver impairment (Child-Pugh A). DALIRESP is not recommended for use in patients with moderate or severe liver impairment (Child-Pugh B or C) [see Contraindications (4) and Clinical Pharmacology (12.3)].

8.7 Renal Impairment

In twelve subjects with severe renal impairment administered a single dose of 500 mcg roflumilast, the AUCs of roflumilast and roflumilast N-oxide were decreased by 21% and 7%, respectively and Cmax were reduced by 16% and 12%, respectively. No dosage adjustment is necessary for patients with renal impairment [see Clinical Pharmacology (12.3)].

10 OVERDOSAGE

10.1 Human Experience

No case of overdose has been reported in clinical studies with DALIRESP. During the Phase I studies of DALIRESP, the following symptoms were observed at an increased rate after a single oral dose of 2500 mcg and a single dose of 5000 mcg: headache, gastrointestinal disorders, dizziness, palpitations, lightheadedness, clamminess, and arterial hypotension.

10.2 Management of Overdose

In case of overdose, patients should seek immediate medical help. Appropriate supportive medical care should be provided. Since roflumilast is highly protein bound, hemodialysis is not likely to be an efficient method of drug removal. It is not known whether roflumilast is dialyzable by peritoneal dialysis.

11 DESCRIPTION

The active ingredient in DALIRESP tablets is roflumilast. Roflumilast and its active metabolite (roflumilast N-oxide) are selective phosphodiesterase 4 (PDE4) inhibitors. The chemical name of roflumilast is N-(3,5-dichloropyridin-4-yl)-3-cyclopropylmethoxy-4-difluoromethoxy-benzamide. Its empirical formula is C17H14Cl2F2N2O3 and the molecular weight is 403.22.

The chemical structure is:

The drug substance is a white to off-white non-hygroscopic powder with a melting point of 160°C. It is practically insoluble in water and hexane, sparingly soluble in ethanol, and freely soluble in acetone.

DALIRESP is supplied as white to off-white, round tablets, embossed with “D” on one side and “250” or “500” on the other side. Each tablet contains 250 mcg or 500 mcg of roflumilast.

Each tablet of DALIRESP for oral administration contains the following inactive ingredients: lactose monohydrate, corn starch, povidone, and magnesium stearate.

12 CLINICAL PHARMACOLOGY

12.1 Mechanism of Action

Roflumilast and its active metabolite (roflumilast N-oxide) are selective inhibitors of phosphodiesterase 4 (PDE4). Roflumilast and roflumilast N-oxide inhibition of PDE4 (a major cyclic-3′,5′-adenosine monophosphate (cyclic AMP)-metabolizing enzyme in lung tissue) activity leads to accumulation of intracellular cyclic AMP. While the specific mechanism(s) by which DALIRESP exerts its therapeutic action in COPD patients is not well defined, it is thought to be related to the effects of increased intracellular cyclic AMP in lung cells.

12.2 Pharmacodynamics

In COPD patients, 4‑week treatment with DALIRESP 500 mcg oral once daily reduced sputum neutrophils and eosinophils by 31%, and 42%, respectively. In a pharmacodynamic study in healthy volunteers, DALIRESP 500 mcg once daily reduced the number of total cells, neutrophils and eosinophils found in bronchoalveolar lavage fluid following segmental pulmonary lipopolysaccharide (LPS) challenge by 35%, 38% and 73%, respectively. The clinical significance of these findings is unknown.

12.3 Pharmacokinetics

Absorption

The absolute bioavailability of roflumilast following a 500 mcg oral dose is approximately 80%. Maximum plasma concentrations (Cmax) of roflumilast typically occur approximately one hour after dosing (ranging from 0.5 to 2 hours) in the fasted state while plateau-like maximum concentrations of the N-oxide metabolite are reached in approximately eight hours (ranging from 4 to 13 hours). Food has no effect on total drug absorption, but delays time to maximum concentration (Tmax) of roflumilast by one hour and reduces Cmax by approximately 40%, however, Cmax and Tmax of roflumilast N-oxide are unaffected. An in vitro study showed that roflumilast and roflumilast N-oxide did not inhibit P-gp transporter.

Distribution

Plasma protein binding of roflumilast and its N-oxide metabolite is approximately 99% and 97%, respectively. Volume of distribution for single‑dose 500 mcg roflumilast is about 2.9 L/kg. Studies in rats with radiolabeled roflumilast indicate low penetration across the blood-brain barrier.

Metabolism

Roflumilast is extensively metabolized via Phase I (cytochrome P450) and Phase II (conjugation) reactions. The N-oxide metabolite is the only major metabolite observed in the plasma of humans. Together, roflumilast and roflumilast N-oxide account for the majority (87.5%) of total dose administered in plasma. In urine, roflumilast was not detectable while roflumilast N-oxide was only a trace metabolite (less than 1%). Other conjugated metabolites such as roflumilast N-oxide glucuronide and 4-amino-3,5-dichloropyridine N-oxide were detected in urine.

While roflumilast is three times more potent than roflumilast N-oxide at inhibition of the PDE4 enzyme in vitro, the plasma AUC of roflumilast N-oxide on average is about 10-fold greater than the plasma AUC of roflumilast.

In vitro studies and clinical drug-drug interaction studies suggest that the biotransformation of roflumilast to its N-oxide metabolite is mediated by CYP1A2 and 3A4. Based on further in vitro results in human liver microsomes, therapeutic plasma concentrations of roflumilast and roflumilast N-oxide do not inhibit CYP1A2, 2A6, 2B6, 2C8, 2C9, 2C19, 2D6, 2E1, 3A4/5, or 4A9/11. Therefore, there is a low probability of relevant interactions with substances metabolized by these P450 enzymes. In addition, in vitro studies demonstrated no induction of the CYP1A2, 2A6, 2C9, 2C19, or 3A4/5 and only a weak induction of CYP2B6 by roflumilast.

Elimination

The plasma clearance after short-term intravenous infusion of roflumilast is on average about 9.6 L/h. Following an oral dose, the median plasma effective half-life of roflumilast and its N-oxide metabolite are approximately 17 and 30 hours, respectively. Steady state plasma concentrations of roflumilast and its N-oxide metabolite are reached after approximately 4 days for roflumilast and 6 days for roflumilast N-oxide following once‑daily dosing. Following intravenous or oral administration of radiolabeled roflumilast, about 70% of the radioactivity was recovered in the urine.

Special Populations

Hepatic Impairment

Roflumilast 250 mcg once daily for 14 days was studied in subjects with mild-to-moderate hepatic impairment classified as Child-Pugh A and B (8 subjects in each group). The AUC of roflumilast and roflumilast N-oxide were increased by 51% and 24%, respectively in Child-Pugh A subjects and by 92% and 41%, respectively, in Child-Pugh B subjects, as compared to age-, weight-, and gender-matched healthy subjects. The Cmax of roflumilast and roflumilast N-oxide were increased by 3% and 26%, respectively, in Child-Pugh A subjects and by 26% and 40%, respectively in Child-Pugh B subjects, as compared to healthy subjects. DALIRESP 500 mcg has not been studied in hepatically impaired patients. Clinicians should consider the risk-benefit of administering DALIRESP to patients who have mild liver impairment (Child-Pugh A). DALIRESP is not recommended for use in patients with moderate or severe liver impairment (Child-Pugh B or C) [see Contraindications (4) and Use in Specific Populations (8.6)].

Renal Impairment

In twelve subjects with severe renal impairment administered a single dose of 500 mcg roflumilast, roflumilast and roflumilast N-oxide AUCs were decreased by 21% and 7%, respectively and Cmax were reduced by 16% and 12%, respectively. No dosage adjustment is necessary for patients with renal impairment [see Use in Specific Populations (8.7)].

Age

Roflumilast 500 mcg once daily for 15 days was studied in young, middle aged, and elderly healthy subjects. The exposure in elderly (>65 years of age) were 27% higher in AUC and 16% higher in Cmax for roflumilast and 19% higher in AUC and 13% higher in Cmax for roflumilast-N-oxide than that in young volunteers (18-45 years old). No dosage adjustment is necessary for elderly patients [see Use in Specific Populations (8.5)].

Gender

In a Phase I study evaluating the effect of age and gender on the pharmacokinetics of roflumilast and roflumilast N-oxide, a 39% and 33% increase in roflumilast and roflumilast N-oxide AUC were noted in healthy female subjects as compared to healthy male subjects. No dosage adjustment is necessary based on gender.

Smoking

The pharmacokinetics of roflumilast and roflumilast N-oxide were comparable in smokers as compared to non-smokers. There was no difference in Cmax between smokers and non-smokers when roflumilast 500 mcg was administered as a single dose to 12 smokers and 12 non-smokers. The AUC of roflumilast in smokers was 13% less than that in non-smokers while the AUC of roflumilast N-oxide in smokers was 17% more than that in non-smokers.

Race

As compared to Caucasians, African Americans, Hispanics, and Japanese showed 16%, 41%, and 15% higher AUC, respectively, for roflumilast and 43%, 27%, and 16% higher AUC, respectively, for roflumilast N-oxide. As compared to Caucasians, African Americans, Hispanics, and Japanese showed 8%, 21%, and 5% higher Cmax, respectively, for roflumilast and 43%, 27%, and 17% higher Cmax, respectively, for roflumilast N-oxide. No dosage adjustment is necessary for race.

Drug Interactions

Drug interaction studies were performed with roflumilast and other drugs likely to be coadministered or drugs commonly used as probes for pharmacokinetic interaction [see Drug Interactions (7)]. No significant drug interactions were observed when 500 mcg oral roflumilast was administered with inhaled salbutamol, formoterol, budesonide and oral montelukast, digoxin, theophylline, warfarin, sildenafil, midazolam, or antacids.

The effect of concomitant drugs on the exposure of roflumilast and roflumilast N-oxide is shown in the Figure 1 below.

Figure 1. Effect of concomitant drugs on the exposure of roflumilast and roflumilast N-oxide. Note that the dashed lines indicate the lower and higher bounds (0.8-1.25) of the 90% confidence interval of the geometric mean ratio of Cmax or AUC for roflumilast or roflumilast N-oxide for Treatment (DALIRESP+Coadministered Drug) vs. Reference (DALIRESP). The dosing regimens of coadministered drugs was: Midazolam: 2 mg po SD; Erythromycin: 500 mg po TID; Ketoconazole: 200 mg po BID; Rifampicin: 600 mg po QD; Fluvoxamine: 50 mg po QD; Digoxin: 250 mcg po SD; Maalox: 30 mL po SD; Salbutamol: 0.2 mg po TID; Cimetidine: 400 mg po BID; Formoterol: 40 mcg po BID; Budesonide: 400 mcg po BID; Theophylline: 375 mg po BID; Warfarin: 250 mg po SD; Enoxacin: 400 mg po BID; Sildenafil: 100 mg SD; Minulet (combination oral contraceptive): 0.075 mg gestodene/0.03 mg ethinylestradiol po QD; Montelukast: 10 mg po QD

Drug interactions considered to be significant are described in more detail below [see Warnings and Precautions (5.4) and Drug Interactions (7)].

Inhibitors of CYP3A4 and CYP1A2:

Erythromycin: In an open-label crossover study in 16 healthy volunteers, the coadministration of CYP3A4 inhibitor erythromycin (500 mg three times daily for 13 days) with a single oral dose of 500 mcg DALIRESP resulted in 40% and 70% increase in Cmax and AUC for roflumilast, respectively, and a 34% decrease and a 4% increase in Cmax and AUC for roflumilast N-oxide, respectively.

Ketoconazole: In an open-label crossover study in 16 healthy volunteers, the coadministration of a strong CYP3A4 inhibitor ketoconazole (200 mg twice daily for 13 days) with a single oral dose of 500 mcg DALIRESP resulted in 23% and 99% increase in Cmax and AUC for roflumilast, respectively, and a 38% reduction and 3% increase in Cmax and AUC for roflumilast N-oxide, respectively.

Fluvoxamine: In an open-label crossover study in 16 healthy volunteers, the coadministration of dual CYP 3A4/1A2 inhibitor fluvoxamine (50 mg daily for 14 days) with a single oral dose of 500 mcg DALIRESP showed a 12% and 156% increase in roflumilast Cmax and AUC along with a 210% decrease and 52% increase in roflumilast N-oxide Cmax and AUC, respectively.

Enoxacin: In an open-label crossover study in 16 healthy volunteers, the coadministration of dual CYP 3A4/1A2 inhibitor enoxacin (400 mg twice daily for 12 days) with a single oral dose of 500 mcg DALIRESP resulted in an increased Cmax and AUC of roflumilast by 20% and 56%, respectively. Roflumilast N-oxide Cmax was decreased by 14% while roflumilast N-oxide AUC was increased by 23%.

Cimetidine: In an open-label crossover study in 16 healthy volunteers, the coadministration of a dual CYP 3A4/1A2 inhibitor cimetidine (400 mg twice daily for 7 days) with a single dose of 500 mcg oral DALIRESP resulted in a 46% and 85% increase in roflumilast Cmax and AUC; and a 4% decrease in Cmax and 27% increase in AUC for roflumilast N-oxide, respectively.

Oral Contraceptives containing Gestodene and Ethinyl Estradiol:

In an open-label crossover study in 20 healthy adult volunteers, coadministration of a single oral dose of 500 mcg DALIRESP with repeated doses of a fixed combination oral contraceptive containing 0.075 mg gestodene and 0.03 mg ethinyl estradiol to steady state caused a 38% increase and 12% decrease in Cmax of roflumilast and roflumilast N-oxide, respectively. Roflumilast and roflumilast N-oxide AUCs were increased by 51% and 14%, respectively.

Inducers of CYP enzymes:

Rifampicin: In an open-label, three-period, fixed-sequence study in 15 healthy volunteers, coadministration of the strong CYP3A4 inducer rifampicin (600 mg once daily for 11 days) with a single oral dose of 500 mcg DALIRESP resulted in reduction of roflumilast Cmax and AUC by 68% and 79%, respectively; and an increase of roflumilast N-oxide Cmax by 30% and reduced roflumilast N-oxide AUC by 56%.

13 NONCLINICAL TOXICOLOGY

13.1 Carcinogenesis, Mutagenesis, Impairment of Fertility

Long-term studies were conducted in hamsters and mice with roflumilast to evaluate its carcinogenic potential. In 2-year oral gavage carcinogenicity studies, roflumilast treatment resulted in dose-related, statistically significant increases in the incidence of undifferentiated carcinomas of nasal epithelium in hamsters at ≥8 mg/kg/day (approximately 11 times the MRHD based on summed AUCs of roflumilast and its metabolites). The tumorigenicity of roflumilast appears to be attributed to a reactive metabolite of 4-amino-3,5-dichloro-pyridine N-oxide (ADCP N-oxide). No evidence of tumorigenicity was observed in mice at roflumilast oral doses up to 12 and 18 mg/kg/day in females and males, respectively (approximately 10 and 15 times the MRHD, respectively, based on summed AUCs of roflumilast and its metabolites).

Roflumilast tested positive in an in vivo mouse micronucleus test, but negative in the following assays: Ames test for bacterial gene mutation, in vitro chromosome aberration assay in human lymphocytes, in vitro HPRT test with V79 cells, an in vitro micronucleus test with V79 cells, DNA adduct formation assay in rat nasal mucosa, liver and testes, and in vivo mouse bone marrow chromosome aberration assay. Roflumilast N-oxide was negative in the Ames test and in vitro micronucleus test with V79 cells.

In a human spermatogenesis study, roflumilast 500 mcg had no effects on semen parameters or reproductive hormones during the 3-month treatment period and the following 3-month off-treatment period. In a fertility study, roflumilast decreased fertility rates in male rats at 1.8 mg/kg/day (approximately 29 times the MRHD on a mg/m^2 basis). The male rats also showed increases in the incidence of tubular atrophy, degeneration in the testis and spermiogenic granuloma in the epididymides. No effect on rat fertility rate or male reproductive organ morphology was observed at 0.6 mg/kg/day (approximately 10 times the MRHD on a mg/m^2 basis). In a female fertility study, no effect on fertility was observed up to the highest roflumilast dose of 1.5 mg/kg/day in rats (approximately 24 times the MRHD on a mg/m^2 basis).

14 CLINICAL STUDIES

14.1 Chronic Obstructive Pulmonary Disease (COPD)

The efficacy and safety of DALIRESP (roflumilast) in COPD was evaluated in 8 randomized, double-blind, controlled, parallel‑group clinical trials in 9394 adult patients (4425 receiving DALIRESP 500 mcg) 40 years of age and older with COPD. Of the 8 trials, two were placebo-controlled dose selection trials (Trials 1 and 2) of 6 months’ duration that evaluated the efficacy of DALIRESP 250 mcg and 500 mcg once daily, four were placebo-controlled 1-year trials (Trials 3, 4, 5, and 6) primarily designed to evaluate the efficacy of DALIRESP on COPD exacerbations, and two were 6-month efficacy trials (Trials 7 and 8) which assessed the effect of DALIRESP as add-on therapy to a long-acting beta agonist or long-acting anti-muscarinic. The 8 trials enrolled patients with nonreversible obstructive lung disease (FEV1/FVC ≤70% and ≤12% or 200 mL improvement in FEV1 in response to 4 puffs of albuterol/salbutamol) but the severity of airflow obstruction at baseline was different among the trials. Patients enrolled in the dose selection trials had the full range of COPD severity (FEV1 30-80% predicted); median age of 63 years, 73% male, and 99% Caucasian. Patients enrolled in the four exacerbation trials had severe COPD (FEV1 ≤50% predicted); median age of 64 years, 74% male, and 90% Caucasian.

Patients enrolled in the two 6-month efficacy trials had moderate to severe COPD (FEV1 40-70% predicted); median age of 65 years, 68% male, and 97% Caucasian. COPD exacerbations and lung function (FEV1) were co-primary efficacy outcome measures in the four 1-year trials. In the two 6-month supportive efficacy trials, lung function (FEV1) alone was the primary efficacy outcome measure.

The two 6-month dose-selection efficacy trials (Trials 1 and 2) explored doses of 250 mcg and 500 mcg once daily in a total of 1929 patients (751 and 724 on DALIRESP 250 and 500 mcg, respectively). The selection of the 500 mcg dose was primarily based on nominal improvements in lung function (FEV1) over the 250 mcg dose. The once‑daily dosing regimen was primarily based on the determination of a plasma half-life of 17 hours for roflumilast and 30 hours for its active metabolite roflumilast N-oxide [see Clinical Pharmacology (12.3)].

An additional placebo-controlled 1-year trial (Trial 9) evaluated the effect of DALIRESP 500 mcg on COPD exacerbations when added to a fixed-dose combination (FDC) product containing an inhaled corticosteroid and long-acting beta agonist (ICS/LABA). At screening, patients were required to have two or more exacerbations in the previous year. This trial randomized a total of 2354 patients (1178 randomized to DALIRESP, 1176 to placebo). Approximately 60% of the patients enrolled had severe COPD (postbronchodilator FEV1 30%-50% of predicted) associated with chronic bronchitis and 39% had very severe COPD (postbronchodilator FEV1 ≤ 30% of predicted) associated with chronic bronchitis; mean age of 64 years, 69% male, and 80% Caucasian. The use of long-acting muscarinic antagonists was allowed.

Effect on Exacerbations

The effect of DALIRESP 500 mcg once daily on COPD exacerbations was evaluated in five 1-year trials (Trials 3, 4, 5, 6 and 9).

Two of the trials (Trials 3 and 4) conducted initially enrolled a population of patients with severe COPD (FEV1 ≤50% of predicted) inclusive of those with chronic bronchitis and/or emphysema who had a history of smoking of at least 10 pack years. Inhaled corticosteroids were allowed as concomitant medications and used in 61% of both DALIRESP and placebo-treated patients and short-acting beta agonists were allowed as rescue therapy. The use of long-acting beta agonists, long-acting anti-muscarinics, and theophylline were prohibited. The rate of moderate or severe COPD exacerbations was a co-primary endpoint in both trials. There was not a symptomatic definition of exacerbation in these 2 trials. Exacerbations were defined in terms of severity requiring treatment with a moderate exacerbation defined as treatment with systemic glucocorticosteroids in Trial 3 or systemic glucocorticosteroids and/or antibiotics in Trial 4 and a severe exacerbation defined as requiring hospitalizations and/or leading to death in Trial 3 or requiring hospitalization in Trial 4. The trials randomized 1176 patients (567 on DALIRESP) in Trial 3 and 1514 patients (760 on DALIRESP) in Trial 4. Both trials failed to demonstrate a significant reduction in the rate of COPD exacerbations.

Exploratory analyses of the results of Trials 3 and 4 identified a subpopulation of patients with severe COPD associated with chronic bronchitis and COPD exacerbations within the previous year that appeared to demonstrate a better response in the reduction of the rate of COPD exacerbations compared to the overall population. As a result, two subsequent trials (Trial 5 and Trial 6) were conducted that enrolled patients with severe COPD but associated with chronic bronchitis, at least one COPD exacerbation in the previous year, and at least a 20 pack-year smoking history. In these trials, long-acting beta agonists and short-acting anti-muscarinics were allowed and were used by 44% and 35% of patients treated with DALIRESP and 45% and 37% of patients treated with placebo, respectively. The use of inhaled corticosteroids was prohibited. As in trials 3 and 4, the rate of moderate exacerbations (defined as requiring intervention with systemic glucocorticosteroids) or severe exacerbations (defined as leading to hospitalization and/or to death) was a co-primary endpoint.

Trial 5 randomized a total of 1525 patients (765 on DALIRESP) and Trial 6 randomized a total of 1571 patients (772 on DALIRESP). In both trials, DALIRESP 500 mcg once daily demonstrated a significant reduction in the rate of moderate or severe exacerbations compared to placebo (Table 2). These two trials provide the evidence to support the use of DALIRESP for the reduction of COPD exacerbations.

Table 2: Effect of DALIRESP on Rate of Moderate or Severe Exacerbations
Study | Exacerbations Per Patient-Year
 | DALIRESP | Placebo | Absolute Reduction [Absolute reduction measured as difference between placebo and roflumilast‑treated patients.] | RR [RR is Rate Ratio.] | 95% CI | Percent Reduction [Percent reduction is defined as 100 (1-RR).]
Trial 5 | 1.1 | 1.3 | 0.2 | 0.85 | 0.74, 0.98 | 15
Trial 6 | 1.2 | 1.5 | 0.3 | 0.82 | 0.71, 0.94 | 18

For patients in Trials 5 and 6 who received concomitant long-acting beta agonists or short-acting anti-muscarinics, reduction of moderate or severe exacerbations with DALIRESP was similar to that observed for the overall populations of the two trials.

In Trial 9, when added to background therapy of FDC ICS/LABA, the rate ratio for COPD exacerbations among patients administered DALIRESP vs. placebo was 0.92 (95% CI 0.81, 1.04).

Effect on Lung Function

While DALIRESP is not a bronchodilator, all 1-year trials (Trials 3, 4, 5, and 6) evaluated the effect of DALIRESP on lung function as determined by the difference in FEV1 between DALIRESP and placebo-treated patients (pre-bronchodilator FEV1 measured prior to study drug administration in three of the trials and post-bronchodilator FEV1 measured 30 minutes after administration of 4 puffs of albuterol/salbutamol in one trial) as a co-primary endpoint. In each of these trials DALIRESP 500 mcg once daily demonstrated a statistically significant improvement in FEV1 which averaged approximately 50 mL across the four trials. Table 3 shows FEV1 results from Trials 5 and 6 which had demonstrated a significant reduction in COPD exacerbations.

Table 3: Effect of DALIRESP on FEV1
Study | Change in FEV1 from Baseline, mL
Trial 5 | DALIRESP | Placebo | Effect [Effect measured as difference between DALIRESP and placebo treated patients.] | 95% CI
Trial 5 | 46 | 8 | 39 | 18, 60
Trial 6 | 33 | -25 | 58 | 41, 75

Lung function was also evaluated in two 6-month trials (Trials 7 and 8) to assess the effect of DALIRESP when administered as add-on therapy to treatment with a long-acting beta agonist or a long-acting anti-muscarinic. These trials were conducted in a different population of COPD patients [moderate to severe COPD (FEV1 40 to 70% of predicted) without a requirement for chronic bronchitis or frequent history of exacerbations] from that for which efficacy in reduction of exacerbations has been demonstrated and provide safety support to the DALIRESP COPD program.

Starting dose titration trial

The tolerability of DALIRESP was evaluated in a 12-week randomized, double-blind, parallel group trial in patients with severe COPD associated with chronic bronchitis (Trial 10). At screening, patients were required to have had at least one exacerbation in the previous year. A total of 1323 patients were randomized to receive DALIRESP 500 mcg once a day for 12 weeks (n=443), DALIRESP 500 mcg every other day for 4 weeks followed by DALIRESP 500 mcg once a day for 8 weeks (n=439), or DALIRESP 250 mcg once a day for 4 weeks followed by DALIRESP 500 mcg once a day for 8 weeks (n=441).

Over the 12-week study period, the percentage of patients discontinuing treatment was 6.2% lower in patients initially receiving DALIRESP 250 mcg daily for 4 weeks followed by DALIRESP 500 mcg daily for 8 weeks (18.4%) compared to those receiving DALIRESP 500 mcg daily for 12 weeks (24.6%) (Odds Ratio = 0.66; 95% CI: 0.47 to 0.93; p=0.017). Because this trial was limited to 12 weeks in duration, whether initiation of dosing with DALIRESP 250 mcg improves the long term tolerability of DALIRESP 500 mcg has not been determined.

16 HOW SUPPLIED/STORAGE AND HANDLING

16.1 How Supplied

DALIRESP 250 mcg is supplied as white to off-white, round tablets, embossed with “D” on one side and “250” on the other side.

DALIRESP 250 mcg tablets are available:

Blister pack 28: NDC 0310-0088-28

2X10 Unit Dose: NDC 0310-0088-39

DALIRESP 500 mcg is supplied as white to off-white, round tablets, embossed with “D” on one side and “500” on the other side.

DALIRESP 500 mcg tablets are available:

Bottles of 30: NDC 0310-0095-30

Bottles of 90: NDC 0310-0095-90

16.2 Storage and Handling

Store DALIRESP tablets at 20° - 25°C (68° - 77°F); excursions permitted to 15° - 30°C (59° - 86°F). [See USP Controlled Room Temperature].

17 PATIENT COUNSELING INFORMATION

Advise the patient to read the FDA-approved patient labeling (Medication Guide).

Bronchospasm

DALIRESP is not a bronchodilator and should not be used for immediate relief of breathing problems (i.e., as a rescue medication).

Psychiatric Events including Suicidality

Treatment with DALIRESP is associated with an increase in psychiatric adverse reactions. Cases of suicidal ideation and behavior, including completed suicide, have been observed in the post-marketing setting in patients with or without a history of depression.

The risks and benefits of treatment with DALIRESP in patients with a history of depression and/or suicidal thoughts or behavior should be carefully considered. Advise patients, caregivers, and families to be alert for the emergence or worsening of insomnia, anxiety, depression, suicidal thoughts or other mood changes, and if such changes occur to contact their healthcare provider so that the risks and benefits of continuing treatment with DALIRESP may be considered [see Warnings and Precautions (5.2)].

Weight Decrease

Weight loss was a common adverse reaction in DALIRESP clinical trials. During follow-up after treatment discontinuation, the majority of patients with weight loss regained some of the weight they had lost while receiving DALIRESP. Advise patients treated with DALIRESP to have their weight monitored regularly. If unexplained weight loss occurs, patients should inform their healthcare provider so that the weight loss can be evaluated, as discontinuation of DALIRESP may need to be considered [see Warnings and Precautions (5.3)].

Drug Interactions

The use of cytochrome P450 enzyme inducers resulted in a reduction in exposure which may result in decreased therapeutic effectiveness of DALIRESP. The use of strong cytochrome P450 enzyme inducers (e.g., rifampicin, phenobarbital, carbamazepine, phenytoin) with DALIRESP is not recommended [see Drug Interactions (7.1) and Clinical Pharmacology (12.3)].

Distributed by:
AstraZeneca Pharmaceuticals LP, Wilmington, DE 19850

Daliresp® is a registered trademark of the AstraZeneca group of companies.

© AstraZeneca 2020

MEDICATION GUIDE

DALIRESP® (da'-li-resp)

(roflumilast)

Tablets

Read this Medication Guide before you start taking DALIRESP® and each time you get a refill. There may be new information. This information does not take the place of talking with your healthcare provider about your medical condition or treatment.

What is the most important information I should know about DALIRESP?

DALIRESP can cause serious side effects. Tell your healthcare provider right away if you have any of the symptoms listed below while taking DALIRESP.

1. DALIRESP may cause mental health problems including suicidal thoughts and behavior. Some people taking DALIRESP may develop mood or behavior problems including:
  1. thoughts of suicide or dying
  2. attempt to commit suicide
  3. trouble sleeping (insomnia)
  4. new or worse anxiety
  5. new or worse depression
  6. acting on dangerous impulses
  7. other unusual changes in your behavior or mood
2. Weight loss. DALIRESP can cause weight loss. You should check your weight on a regular basis. You will also need to see your healthcare provider regularly to have your weight checked. If you notice that you are losing weight, call your healthcare provider. Your healthcare provider may ask you to stop taking DALIRESP if you lose too much weight.

DALIRESP may affect the way other medicines work, and other medicines may affect how DALIRESP works. Tell your healthcare provider about all the medicines you take, including prescription and non-prescription medicines, vitamins, and herbal supplements.

What is DALIRESP?

DALIRESP is a prescription medicine used in adults with severe Chronic Obstructive Pulmonary Disease (COPD) to decrease the number of flare-ups or the worsening of COPD symptoms (exacerbations).

DALIRESP is not a bronchodilator and should not be used for treating sudden breathing problems. Your healthcare provider may give you other medicine to use for sudden breathing problems.

It is not known if DALIRESP is safe and effective in children.

Who should not take DALIRESP?

Do not take DALIRESP if you:

- have certain liver problems. Talk with your healthcare provider before you take DALIRESP if you have liver problems.

What should I tell my healthcare provider before taking DALIRESP?

Before you take DALIRESP, tell your healthcare provider if you:

- have or have had a history of mental health problems including depression and suicidal behavior.
- have liver problems
- have any other medical conditions
- are pregnant or plan to become pregnant. It is not known if DALIRESP will harm your unborn baby. Talk to your healthcare provider if you are pregnant or plan to become pregnant.
- are breastfeeding or plan to breastfeed. It is not known if DALIRESP passes into your breast milk. You and your healthcare provider should decide if you will take DALIRESP or breastfeed. You should not do both.

How should I take DALIRESP?

- Take DALIRESP exactly as your healthcare provider tells you to take it.
- DALIRESP can be taken with or without food.
- If you take more than your prescribed dose of DALIRESP, call your healthcare provider or go to the nearest hospital emergency room right away.

What are the possible side effects of DALIRESP?

DALIRESP can cause serious side effects, including:

See “What is the most important information I should know about DALIRESP?”

The most common side effects of DALIRESP include:

- diarrhea
- weight loss
- nausea
- headache
- back pain
- flu like symptoms
- problems sleeping (insomnia)
- dizziness
- decreased appetite

Tell your healthcare provider if you have any side effect that bothers you or that does not go away.

These are not all the possible side effects of DALIRESP.

Call your doctor for medical advice about side effects. You may report side effects to FDA at 1-800-FDA-1088.

How do I store DALIRESP Tablets?

- Store DALIRESP at 68°F to 77°F (20°C to 25°C); excursions permitted to 15° - 30°C (59° - 86°F). [See USP Controlled Room Temperature].

Keep DALIRESP Tablets and all medicines out of the reach of children.

General information about DALIRESP

Medicines are sometimes prescribed for purposes other than those listed in a Medication Guide. Do not use DALIRESP for a condition for which it was not prescribed. Do not give DALIRESP to other people, even if they have the same symptoms that you have. It may harm them.

This Medication Guide summarizes the most important information about DALIRESP. For more information about DALIRESP, talk with your healthcare provider. You can ask your healthcare provider or pharmacist for information about DALIRESP that is written for health professionals.

For more information about DALIRESP call 1-800-236-9933.

What are the ingredients in DALIRESP?

Active ingredient: roflumilast
Inactive ingredients: lactose monohydrate, corn starch, povidone and magnesium stearate.

This Medication Guide has been approved by the U.S. Food and Drug Administration.

Rev. 04/2017

Distributed by:
AstraZeneca Pharmaceuticals LP, Wilmington, DE 19850

PACKAGE/LABEL PRINCIPAL DISPLAY PANEL – 250 mcg

Rx Only 28 Tablets NDC 0310-0088-28

Daliresp®

(roflumilast) tablets 250 mcg

28 Day Pack

CONTENTS: One Child-Resistant Package containing 28 tablets

AstraZeneca

PACKAGE/LABEL PRINCIPAL DISPLAY PANEL – 500 mcg

Rx Only NDC 0310-0095-30

Daliresp®

(roflumilast) tablets

500 mcg per tablet

Dispense the accompanying

Medication Guide to each patient

30 Tablets

AstraZeneca